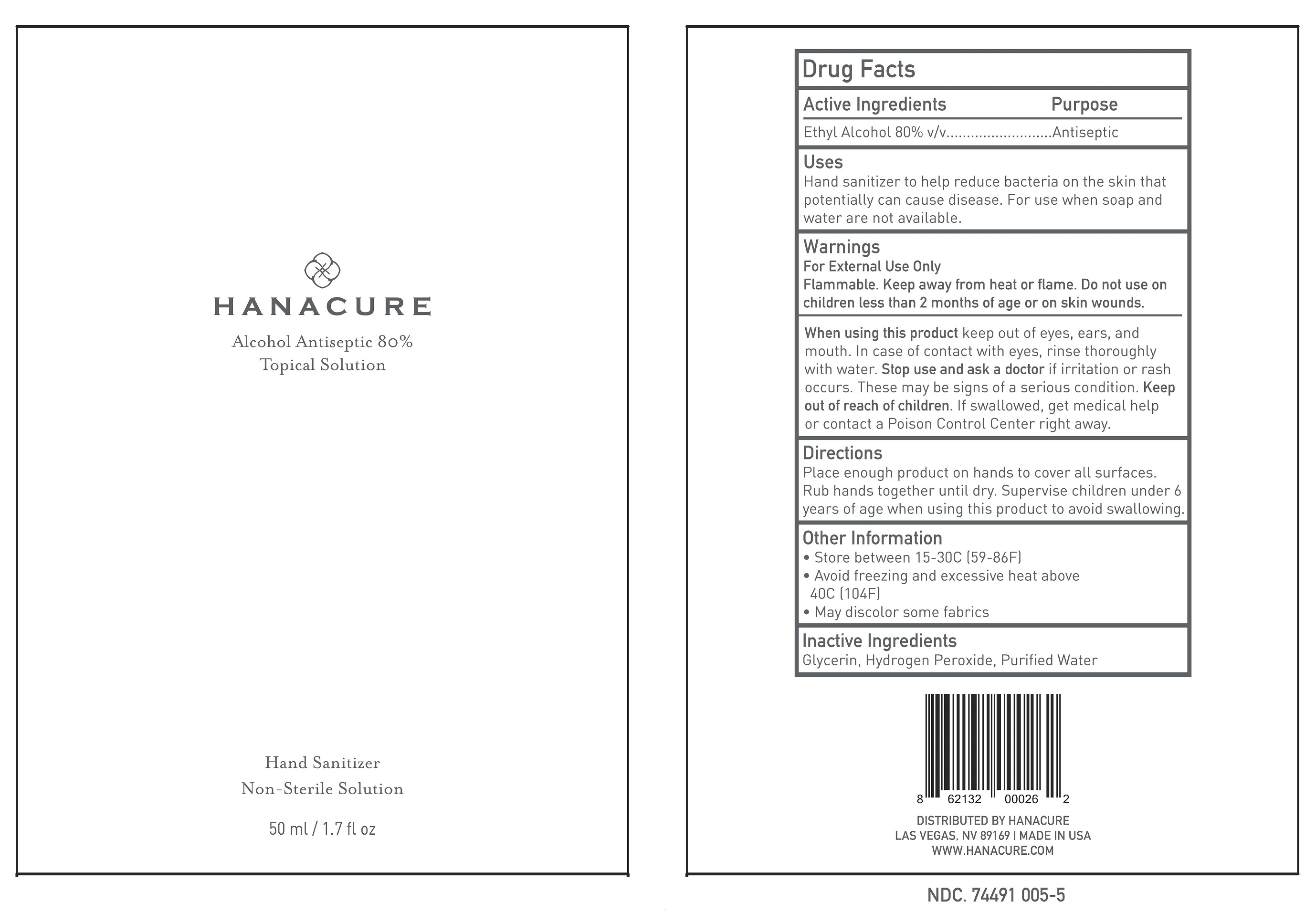 DRUG LABEL: Hanacure Hand Sanitizer
NDC: 74491-0005 | Form: SOLUTION
Manufacturer: Ambrosia Frangrance
Category: otc | Type: HUMAN OTC DRUG LABEL
Date: 20200618

ACTIVE INGREDIENTS: ALCOHOL 80 L/100 L
INACTIVE INGREDIENTS: GLYCERIN; HYDROGEN PEROXIDE; WATER

Active Ingredient(s)

Alcohol 80% v/v. Purpose: Antiseptic

Purpose

Antiseptic, Hand Sanitizer

Use

Hand Sanitizer to help reduce bacteria on the skin that potentially can cause disease. For use when soap and water are not available.

Warnings

For external use only.

Flammable. Keep away from heat or flame.

Do not use

on children less than 2 months of age or on open skin wounds.

When using this product keep out of eyes, ears, and mouth. In case of contact with eyes, rinse thoroughly with water.

Stop use and ask a doctor if irritation or rash occurs. These may be signs of a serious condition.

Keep out of reach of children. If swallowed, get medical help or contact a Poison Control Center right away.

Directions

Place enough product on hands to cover all surfaces.

Rub hands together until dry. Supervise children under 6 years of age when using this product to avoid swallowing.

Other information

- Store between 15-30C (59-86F)
- Avoid freezing and excessive heat above 40C (104F)
- May discolor some fabrics

Inactive ingredients

Glycerin, Hydrogen Peroxide, Purified Water